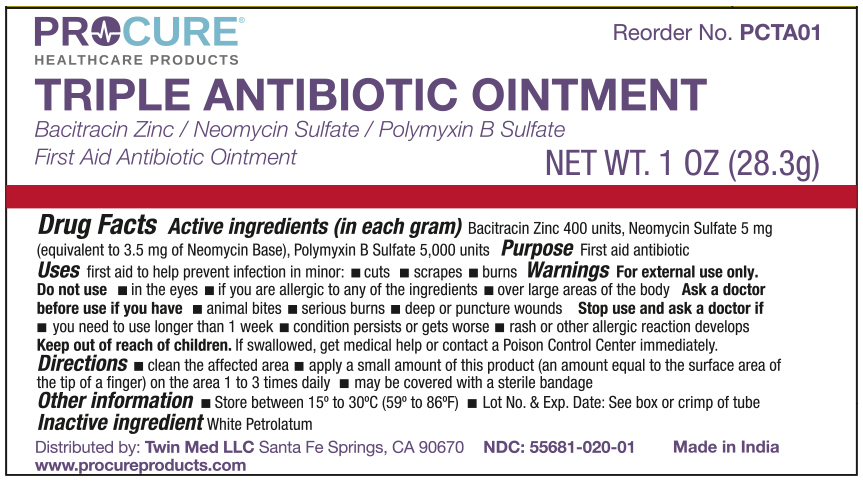 DRUG LABEL: ProCure Triple Antibiotic
NDC: 55681-020 | Form: OINTMENT
Manufacturer: Twin Med LLC
Category: otc | Type: HUMAN OTC DRUG LABEL
Date: 20250616

ACTIVE INGREDIENTS: POLYMYXIN B SULFATE 5000 [iU]/1 g; NEOMYCIN SULFATE 5 mg/1 g; BACITRACIN ZINC 400 [iU]/1 g
INACTIVE INGREDIENTS: WHITE PETROLATUM

Active Ingredients

Bacitracin Zinc 400 units

Neomycin Sulfate 5 mg (equilvant to 3.5mg of Neomycin Base)

Polymyxin B Sulfate 5,000 units

Purpose

First Aid Antibiotic

Uses

First aid to help prevent infection in minor:

- cuts
- scrapes
- burns

Warnings

For External Use Only

Do not use

- in the eyes
- if you are allergic to any of the ingredients
- over large areas of the body

Ask a doctor before use if you have:

- animal bites
- serious burns
- deep or puncture wounds

Keep out of reach of children. if swallowed, get medical help or contact a Poison Control Center immediately.

Directions

- clean the affected area
- apply a small amount of this product (an amount equal to the surface area of the tip of a finger) on the area 1 to 3 times daily
- may be covered with a sterile bandage

Inactive Ingredient

Inactive Ingredient: White Petrolatum